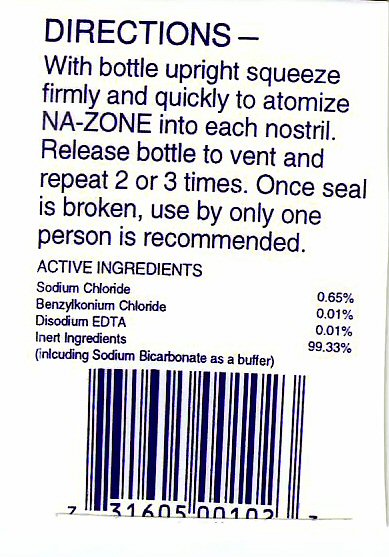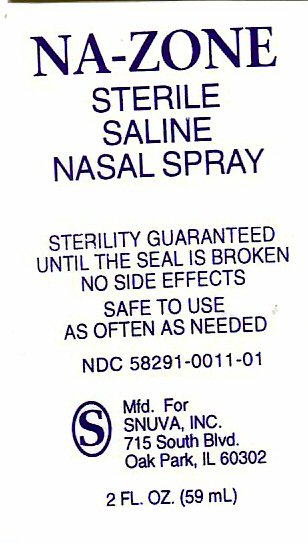 DRUG LABEL: NA-ZONE
NDC: 58291-0011 | Form: LOTION
Manufacturer: Snuva, Inc.
Category: otc | Type: HUMAN OTC DRUG LABEL
Date: 20101123

ACTIVE INGREDIENTS: SODIUM CHLORIDE .65 mL/100 mL
INACTIVE INGREDIENTS: WATER; EDETATE DISODIUM; BENZALKONIUM CHLORIDE; SODIUM BICARBONATE

ACTIVE INGREDIENT

SODIUM CHLORIDE

INACTIVE INGREDIENTS

BENZALKONIUM CHLORIDE

DISODIUM EDTA

DEIONIZED WATER

SODIUM BICARBONATE

PURPOSE

STERILE SALINE NASAL SPRAY

USE

SAFETY TO USE AS OFTEN AS NEEDED

KEEP OUT OF REACH OF CHILDREN

Enter section text here

DIRECTIONS

DIRECTIONS - WITH BOTTLE UPRIGHT SQUEEZE FIRMLY AND QUICKLY TO ATOMIZE NA-ZONE INTO EACH NOSTRIL. RELEASE BOTTLE TO VENT AND REPEAT 2 OR 3 TIMES

WARNINGS

STERILITY GUARANTEED UNTIL THE SEAL IS BROKEN. NO SIDE EFFECTS ONCE SEAL IS BROKEN USE BY ONLY ONE PERSON IS RECOMMENDED

NA-ZONE LABEL

NA-ZONE STERILE SALINE NASAL SPRAY
MANUFACTURED FOR SNUVA INC 715 SOUTH BLVD OAK PARK IL 2 FL OZ (59 ml)